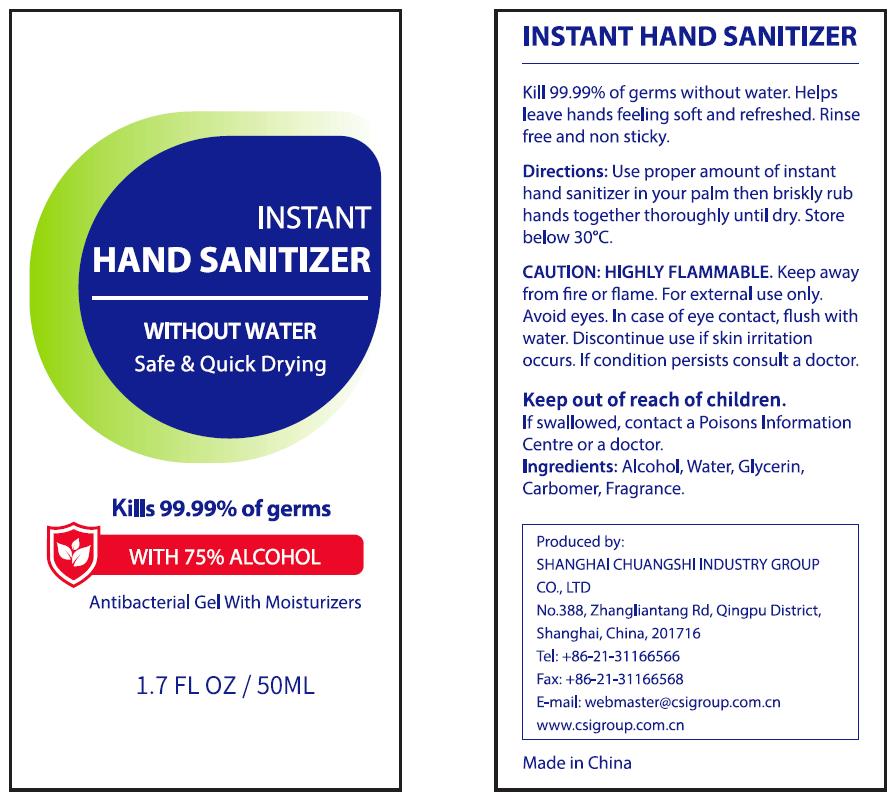 DRUG LABEL: INSTANT HAND SANITIZER
NDC: 73557-220 | Form: SOLUTION, CONCENTRATE
Manufacturer: Shanghai Chuangshi Industry Group Co., Ltd
Category: otc | Type: HUMAN OTC DRUG LABEL
Date: 20200319

ACTIVE INGREDIENTS: ALCOHOL 37.5 mL/50 mL
INACTIVE INGREDIENTS: GLYCERIN 0.25 mL/50 mL; WATER 11.925 mL/50 mL; CARBOMER HOMOPOLYMER, UNSPECIFIED TYPE 0.3 mL/50 mL; CLOVE 0.025 mL/50 mL

Instant Hand Sanitizer, 50mL

Active ingredient

Alcohol

Inactive ingredient

Water
Carbomer
Glycerin
Fragrance

Purpose

Kill 99.9% germs without water.

Helps leave hands feeling soft and refreshed.

Rinse free and non sticky.

When using

Kill 99.9% germs without water.

Helps leave hands feeling soft and refreshed.

Do not use if beyonding directions.

Stop use

Discontinue use if skin irritaion occurs.

Ask doctor

Discontinue use if skin irritaion occurs. If condition persists consult a doctor.

Ask doctor/pharmacist

Discontinue use if skin irritaion occurs. If condition persists consult a doctor or pharmacist.

Keep out of reach of children

Questions

Please contact with us at the phone number +86-21-31166566 when you have any questions.

Pregnancy or breast feeding

Pregnant or breast feeding women shall follow doctor advice.

Indications & usage

Use proper amount of instant hand sanitizer in your palm then brisky rub hands together thoroughly until dry.

Store below 30oC.

Dosage & administration

Use it as needed, after following the usage instructions.

For external use only.

Dosage forms & strengths

This product is gel dosage form.
The active ingredient strength is 50%.

Warnings

HIGHLY FLAMMABLE. Keep away from fire or flame.

For external use only.

Avoid eyes. In case of eye contact, flush with water.

Discontinue use if skin irritaion occurs. If condition persists consult a doctor.